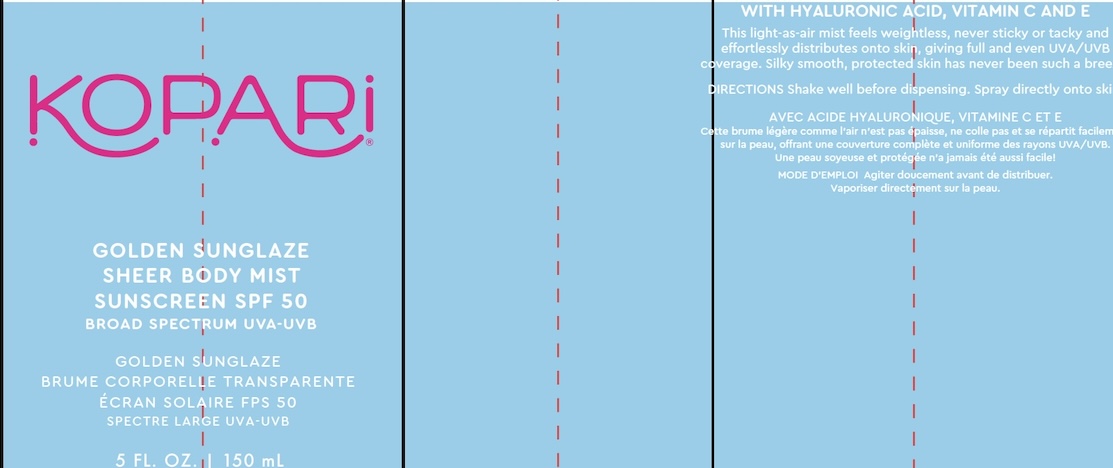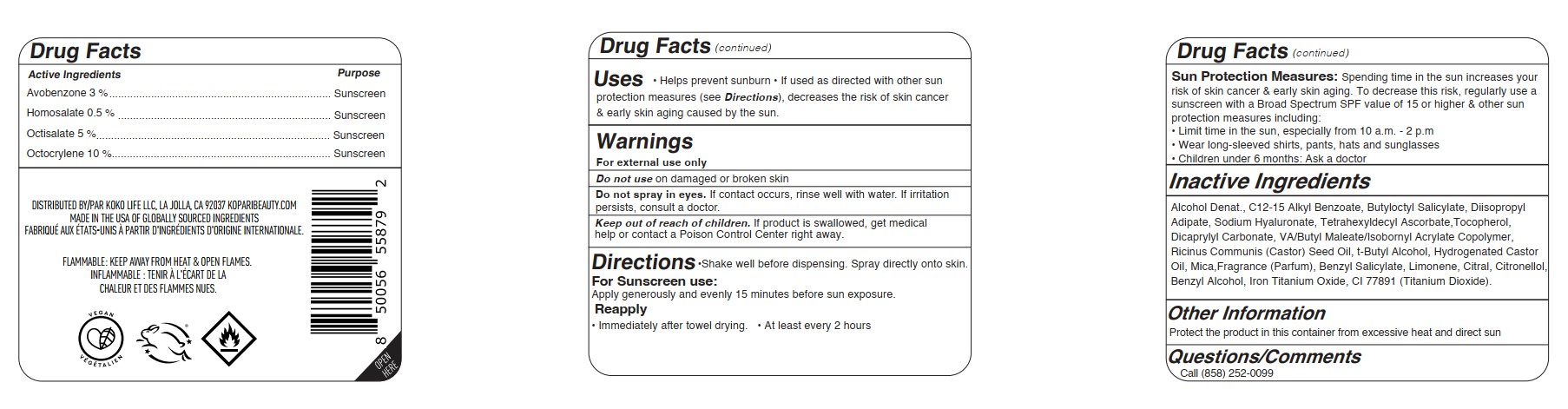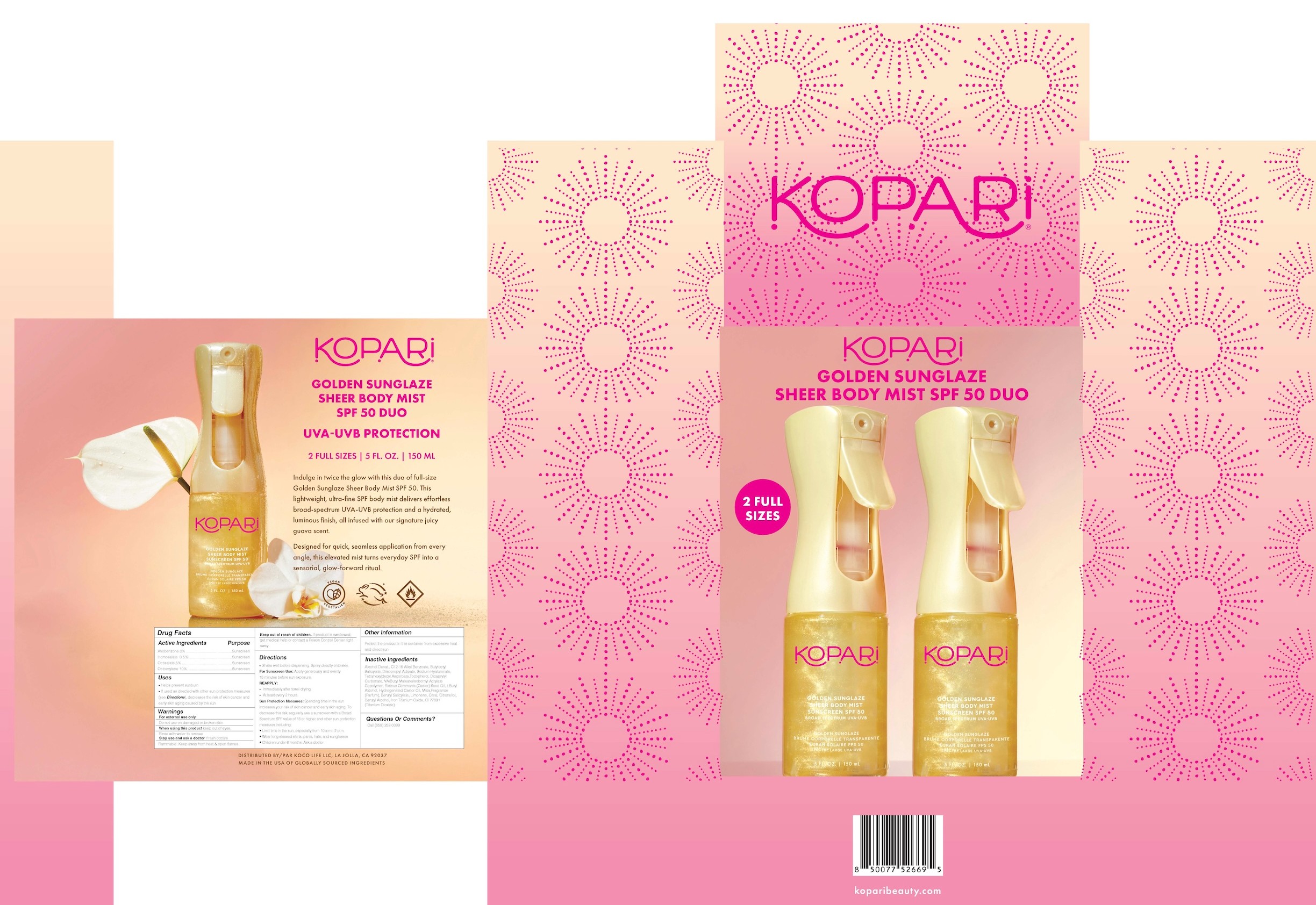 DRUG LABEL: Golden Sunglaze Sheer Body Mist Sunscreen SPF50
NDC: 84130-012 | Form: SPRAY
Manufacturer: Koco Life LLC
Category: otc | Type: HUMAN OTC DRUG LABEL
Date: 20260205

ACTIVE INGREDIENTS: AVOBENZONE 30 mg/1 mL; HOMOSALATE 5 mg/1 mL; OCTISALATE 50 mg/1 mL; OCTOCRYLENE 100 mg/1 mL
INACTIVE INGREDIENTS: ALKYL (C12-15) BENZOATE; TOCOPHEROL; DIISOPROPYL ADIPATE; ISOBORNYL ACRYLATE; CASTOR OIL; HYDROGENATED CASTOR OIL; TITANIUM DIOXIDE; .BETA.-CITRONELLOL, (R)-; LIMONENE, (+)-; ALCOHOL; BUTYLOCTYL SALICYLATE; TETRAHEXYLDECYL ASCORBATE; CITRAL; TERT-BUTYL ALCOHOL; HYALURONATE SODIUM; DICAPRYLYL CARBONATE; MICA; BENZYL SALICYLATE; BENZYL ALCOHOL

Golden Sunglaze Sheer Body Mist Sunscreen SPF50

Active Ingredients

Avobenzone 3 %

Homosalate 0.5 %

Octisalate 5 %

Octocrylene 10 %

Purpose

Avobenzone 3 %...................Sunscreen

Homosalate 0.5 %...................Sunscreen

Octisalate 5 %...................Sunscreen

Octocrylene 10 %...................Sunscreen

Uses

• Helps prevent sunburn

• If used as directed with other sunprotection measures (see Directions), decreases the risk of skin cancer & early skin aging caused by the sun.

Warnings

For external use only

Do not use on damaged or broken skin

WHEN USING

Do not spray in eyes. If contact occurs, rinse well with water. If irritation persists, consult a doctor

Keep out of reach of children. If product is swallowed, get medical help or contact a Poison Control Center right away.

Directions

•Shake well before dispensing. Spray directly onto skin.

For Sunscreen use: Apply generously and evenly 15 minutes before sun exposure.

Reapply • Immediately after towel drying. • At least every 2 hours

Sun Protection Measures: Spending time in the sun increases yourrisk of skin cancer & early skin aging. To decrease this risk, regularly use a sunscreen with a Broad Spectrum SPF value of 15 or higher & other sun protection measures including:

• Limit time in the sun, especially from 10 a.m. - 2 p.m

• Wear long-sleeved shirts, pants, hats and sunglasses

• Children under 6 months: Ask a doctor

Inactive Ingredients

Alcohol Denat., C12-15 Alkyl Benzoate, Butyloctyl Salicylate, Diisopropyl Adipate, Sodium Hyaluronate, Tetrahexyldecyl Ascorbate,Tocopherol, Dicaprylyl Carbonate, VA/Butyl Maleate/Isobornyl Acrylate Copolymer, Ricinus Communis (Castor) Seed Oil, t-Butyl Alcohol, Hydrogenated Castor Oil, Mica,Fragrance (Parfum), Benzyl Salicylate, Limonene, Citral, Citronellol, Benzyl Alcohol, Iron Titanium Oxide, CI 77891 (Titanium Dioxide).

Other Information

Protect the product in this container from excessive heat and direct sun

Questions/Comments

Call (858) 252-0099

PACKAGE LABEL

Kopari

Golden Sunglaze

Sheer Body Mist

Sunscreen SPF 50

Broad Spectrum UVA-UVB

5 Fl. Oz. | 150 mL